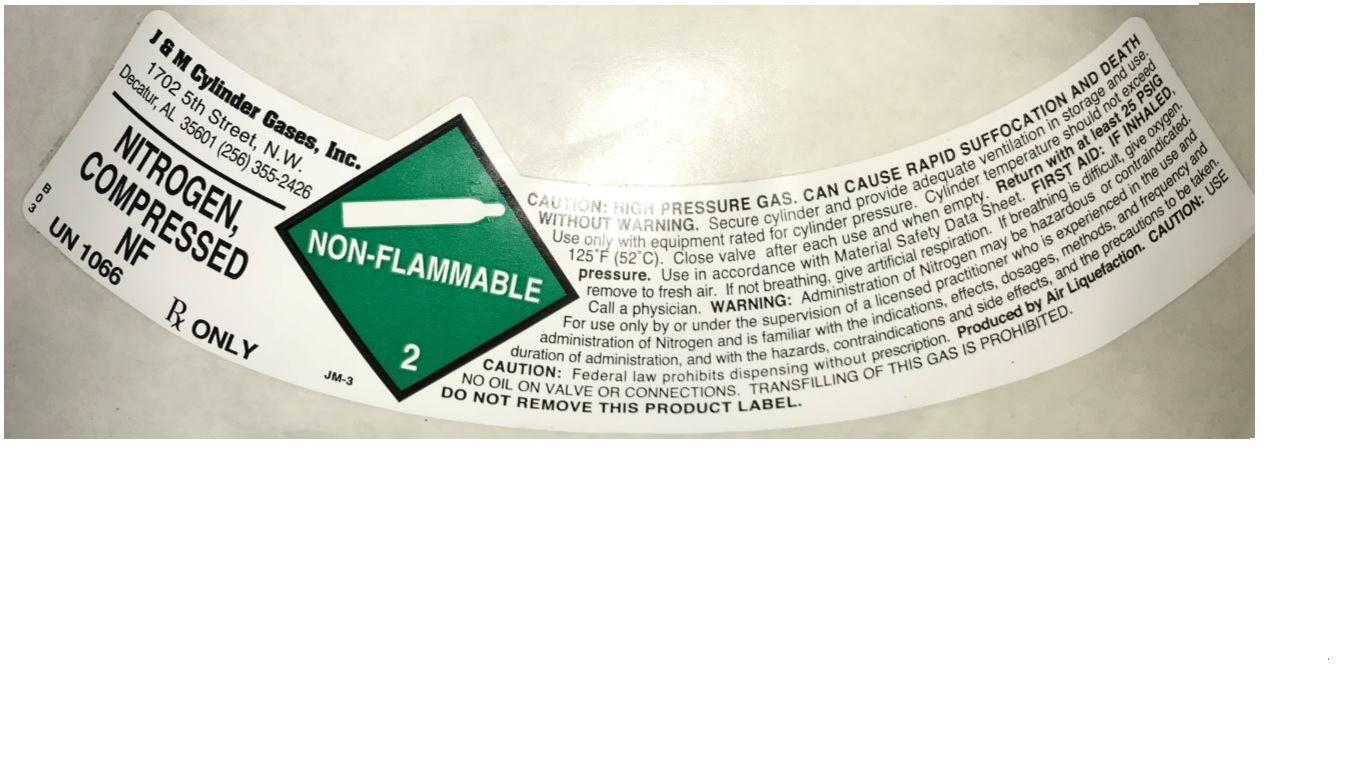 DRUG LABEL: Nitrogen
NDC: 63862-003 | Form: GAS
Manufacturer: J & M CYLINDER GASES, INC.
Category: prescription | Type: HUMAN PRESCRIPTION DRUG LABEL
Date: 20251029

ACTIVE INGREDIENTS: NITROGEN 990 mL/1 L

nitrogen

PACKAGE LABEL

J & M Cylinder Gases, Inc.

1702 5TH STREET N.W.

DECATUR, AL 35601 (256) 355-2426

NITROGEN, COMPRESSED NF

UN1066

Rx ONLY

CAUTION: HIGH PRESSURE GAS. CAN CAUSE RAPID SUFFOCATION AND DEATH WITHOUT WARNING. Secure cylinder and provide adequate ventilation in storage and use. Use only with equipment rated for cylinder pressure. Cylinder temperature should not exceed 125 F (52 C). Close valve after each use and when empty. Return with at least 25 PSIG pressure. Use in accordance with Material Safety Data Sheet. FIRST AID: IF INHALED, remove to fresh air. If not breathing, give artificial respiration. If breathing is difficult, give oxygen. Call a physician. WARNING: Administration of Nitrogen may be hazardous or contraindicated. For use only by or under the supervision of a licensed practitioner who is experienced in the use and administration of Nitrogen and is familiar with the indications, effects, dosages, methods, and frequency and duration of administration, and with the hazards, contraindications and side effects, and the precautions to be taken. CAUTION: Federal law prohibits dispensing with prescription. Produced by Air Liquefaction. CAUTION: USE NOT OIL ON VALVE OR CONNECTIONS. TRANSFILLING OF THIS GAS IS PROHIBITED.

DO NOT REMOVE THIS PRODUCT LABEL.